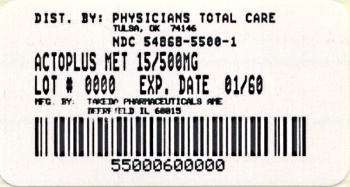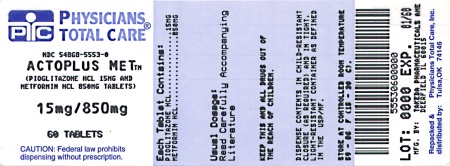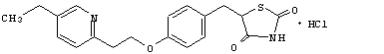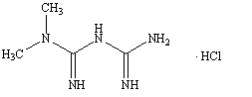 DRUG LABEL: Actoplus Met
NDC: 54868-5500 | Form: TABLET, FILM COATED
Manufacturer: Physicians Total Care, Inc.
Category: prescription | Type: HUMAN PRESCRIPTION DRUG LABEL
Date: 20100224

ACTIVE INGREDIENTS: PIOGLITAZONE HYDROCHLORIDE 15 mg/1 1; METFORMIN HYDROCHLORIDE 500 mg/1 1
INACTIVE INGREDIENTS: POVIDONE; CELLULOSE, MICROCRYSTALLINE; CROSCARMELLOSE SODIUM; MAGNESIUM STEARATE; POLYETHYLENE GLYCOL 8000; TITANIUM DIOXIDE; TALC

ACTOPLUS MET®
(pioglitazone hydrochloride and metformin hydrochloride) tablets

WARNING: CONGESTIVE HEART FAILURE

- Thiazolidinediones, including pioglitazone, which is a component of ACTOPLUS MET, cause or exacerbate congestive heart failure in some patients (see WARNINGS, Pioglitazone hydrochloride). After initiation of ACTOPLUS MET, and after dose increases, observe patients carefully for signs and symptoms of heart failure (including excessive, rapid weight gain, dyspnea, and/or edema). If these signs and symptoms develop, the heart failure should be managed according to the current standards of care. Furthermore, discontinuation or dose reduction of ACTOPLUS MET must be considered.
- ACTOPLUS MET is not recommended in patients with symptomatic heart failure. Initiation of ACTOPLUS MET in patients with established NYHA Class III or IV heart failure is contraindicated (see CONTRAINDICATIONS and WARNINGS, Pioglitazone hydrochloride).

DESCRIPTION

ACTOPLUS MET® (pioglitazone hydrochloride and metformin hydrochloride) tablets contain two oral antihyperglycemic drugs used in the management of type 2 diabetes: pioglitazone hydrochloride and metformin hydrochloride. The concomitant use of pioglitazone and metformin has been previously approved based on clinical trials in patients with type 2 diabetes inadequately controlled on metformin. Additional efficacy and safety information about pioglitazone and metformin monotherapies may be found in the prescribing information for each individual drug.

Pioglitazone hydrochloride is an oral antihyperglycemic agent that acts primarily by decreasing insulin resistance. Pioglitazone is used in the management of type 2 diabetes. Pharmacological studies indicate that pioglitazone improves sensitivity to insulin in muscle and adipose tissue and inhibits hepatic gluconeogenesis. Pioglitazone improves glycemic control while reducing circulating insulin levels.

Pioglitazone [(±)-5-[[4-[2-(5-ethyl-2-pyridinyl)ethoxy]phenyl]methyl]-2,4-] thiazolidinedione monohydrochloride belongs to a different chemical class and has a different pharmacological action than the sulfonylureas, biguanides, or the α-glucosidase inhibitors. The molecule contains one asymmetric center, and the synthetic compound is a racemate. The two enantiomers of pioglitazone interconvert in vivo. The structural formula is as shown:

pioglitazone hydrochloride

Pioglitazone hydrochloride is an odorless white crystalline powder that has a molecular formula of C19H20N2O3S•HCl and a molecular weight of 392.90. It is soluble in N,N-dimethylformamide, slightly soluble in anhydrous ethanol, very slightly soluble in acetone and acetonitrile, practically insoluble in water, and insoluble in ether.

Metformin hydrochloride (N,N -dimethylimidodicarbonimidic diamide hydrochloride) is not chemically or pharmacologically related to any other classes of oral antihyperglycemic agents. Metformin hydrochloride is a white crystalline powder with a molecular formula of C4H11N5•HCl and a molecular weight of 165.62. Metformin hydrochloride is freely soluble in water and is practically insoluble in acetone, ether, and chloroform. The pKa of metformin is 12.4. The pH of a 1% aqueous solution of metformin hydrochloride is 6.68. The structural formula is as shown:

metformin hydrochloride

ACTOPLUS MET is available as a tablet for oral administration containing 15 mg pioglitazone hydrochloride (as the base) with 500 mg metformin hydrochloride (15 mg/500 mg) or 15 mg pioglitazone hydrochloride (as the base) with 850 mg metformin hydrochloride (15 mg/850 mg) formulated with the following excipients: povidone USP, microcrystalline cellulose NF, croscarmellose sodium NF, magnesium stearate NF, hypromellose 2910 USP, polyethylene glycol 8000 NF, titanium dioxide USP, and talc USP.

CLINICAL PHARMACOLOGY

Mechanism of Action

ACTOPLUS MET

ACTOPLUS MET combines two antihyperglycemic agents with different mechanisms of action to improve glycemic control in patients with type 2 diabetes: pioglitazone hydrochloride, a member of the thiazolidinedione class, and metformin hydrochloride, a member of the biguanide class. Thiazolidinediones are insulin-sensitizing agents that act primarily by enhancing peripheral glucose utilization, whereas biguanides act primarily by decreasing endogenous hepatic glucose production.

Pioglitazone hydrochloride

Pioglitazone depends on the presence of insulin for its mechanism of action. Pioglitazone decreases insulin resistance in the periphery and in the liver resulting in increased insulin-dependent glucose disposal and decreased hepatic glucose output. Unlike sulfonylureas, pioglitazone is not an insulin secretagogue. Pioglitazone is a potent and highly selective agonist for peroxisome proliferator-activated receptor-gamma (PPARγ). PPAR receptors are found in tissues important for insulin action such as adipose tissue, skeletal muscle, and liver. Activation of PPARγ nuclear receptors modulates the transcription of a number of insulin responsive genes involved in the control of glucose and lipid metabolism.

In animal models of diabetes, pioglitazone reduces the hyperglycemia, hyperinsulinemia, and hypertriglyceridemia characteristic of insulin-resistant states such as type 2 diabetes. The metabolic changes produced by pioglitazone result in increased responsiveness of insulin-dependent tissues and are observed in numerous animal models of insulin resistance.

Since pioglitazone enhances the effects of circulating insulin (by decreasing insulin resistance), it does not lower blood glucose in animal models that lack endogenous insulin.

Metformin hydrochloride

Metformin hydrochloride improves glucose tolerance in patients with type 2 diabetes, lowering both basal and postprandial plasma glucose. Metformin decreases hepatic glucose production, decreases intestinal absorption of glucose and improves insulin sensitivity by increasing peripheral glucose uptake and utilization. Unlike sulfonylureas, metformin does not produce hypoglycemia in either patients with type 2 diabetes or normal subjects (except in special circumstances, see PRECAUTIONS, General: Metformin hydrochloride) and does not cause hyperinsulinemia. With metformin therapy, insulin secretion remains unchanged while fasting insulin levels and day-long plasma insulin response may actually decrease.

Pharmacokinetics and Drug Metabolism

Absorption and Bioavailability:

ACTOPLUS MET

In bioequivalence studies of ACTOPLUS MET 15 mg/500 mg and 15 mg/850 mg, the area under the curve (AUC) and maximum concentration (Cmax) of both the pioglitazone and the metformin component following a single dose of the combination tablet were bioequivalent to ACTOS® 15 mg concomitantly administered with Glucophage® (500 mg or 850 mg respectively) tablets under fasted conditions in healthy subjects (Table 1).

Table 1. Mean (SD) Pharmacokinetic Parameters for ACTOPLUS MET®
Regimen | N | AUC(0-inf) (ng∙ h/mL) |  | N | Cmax (ng/mL) | N |  | Tmax (h) | N | T1/2 (h)
pioglitazone HCl
15 mg/500 mg ACTOPLUS MET® | 51 | 5984 (1599) | 63 |  | 585 (198) |  | 63 | 1.83 (0.93) | 51 | 8.69 (3.86)
15 mg ACTOS® and 500 mg Glucophage® | 54 | 5810 (1472) | 63 |  | 608 (204) |  | 63 | 1.75 (0.90) | 54 | 7.90 (3.08)
15 mg/850 mg ACTOPLUS MET® | 52 | 5671 (1585) | 60 |  | 569 (222) |  | 60 | 1.89 (0.80) | 52 | 7.19 (1.84)
15 mg ACTOS® and 850 mg Glucophage® | 55 | 5957 (1680) | 61 |  | 603 (239) |  | 61 | 2.01 (1.54) | 55 | 7.16 (1.85)
metformin HCl
15 mg/500 mg ACTOPLUS MET® | 59 | 7783 (2266) | 63 |  | 1203 (325) |  | 63 | 2.32 (0.88) | 59 | 8.57 (14.30)
15 mg ACTOS® and 500 mg Glucophage® | 59 | 7599 (2385) | 63 |  | 1215 (329) |  | 63 | 2.53 (0.95) | 59 | 6.73 (5.87)
15 mg/850 mg ACTOPLUS MET® | 47 | 11927 (3311) | 60 |  | 1827 (536) |  | 60 | 2.41 (0.91) | 47 | 17.56 (20.08)
15 mg ACTOS® and 850 mg Glucophage® | 52 | 11569 (3494) | 61 |  | 1797 (525) |  | 61 | 2.26 (0.85) | 52 | 17.01 (18.09)

Administration of ACTOPLUS MET 15 mg/850 mg with food resulted in no change in overall exposure of pioglitazone. With metformin there was no change in AUC; however mean peak serum concentration of metformin was decreased by 28% when administered with food. A delayed time to peak serum concentration was observed for both components (1.9 hours for pioglitazone and 0.8 hours for metformin) under fed conditions. These changes are not likely to be clinically significant.

Pioglitazone hydrochloride

Following oral administration, in the fasting state, pioglitazone is first measurable in serum within 30 minutes, with peak concentrations observed within 2 hours. Food slightly delays the time to peak serum concentration to 3 to 4 hours, but does not alter the extent of absorption.

Metformin hydrochloride

The absolute bioavailability of a 500 mg metformin tablet given under fasting conditions is approximately 50% - 60%. Studies using single oral doses of metformin tablets of 500 mg to 1500 mg, and 850 mg to 2550 mg, indicate that there is a lack of dose proportionality with increasing doses, which is due to decreased absorption rather than an alteration in elimination. Food decreases the extent of and slightly delays the absorption of metformin, as shown by approximately a 40% lower mean peak plasma concentration, a 25% lower AUC in plasma concentration versus time curve, and a 35 minute prolongation of time to peak plasma concentration following administration of a single 850 mg tablet of metformin with food, compared to the same tablet strength administered fasting. The clinical relevance of these decreases is unknown.

Distribution:

Pioglitazone hydrochloride

The mean apparent volume of distribution (V/F) of pioglitazone following single-dose administration is 0.63 ± 0.41 (mean ± SD) L/kg of body weight. Pioglitazone is extensively protein bound (> 99%) in human serum, principally to serum albumin. Pioglitazone also binds to other serum proteins, but with lower affinity. Metabolites M-III and M-IV also are extensively bound (> 98%) to serum albumin.

Metformin hydrochloride

The apparent volume of distribution (V/F) of metformin following single oral doses of 850 mg averaged 654 ± 358 L. Metformin is negligibly bound to plasma proteins. Metformin partitions into erythrocytes, most likely as a function of time. At usual clinical doses and dosing schedules of metformin, steady-state plasma concentrations of metformin are reached within 24 - 48 hours and are generally <1 µg/mL. During controlled clinical trials, maximum metformin plasma levels did not exceed 5 µg/mL, even at maximum doses.

Metabolism, Elimination and Excretion:

Pioglitazone hydrochloride

Pioglitazone is extensively metabolized by hydroxylation and oxidation; the metabolites also partly convert to glucuronide or sulfate conjugates. Metabolites M-II and M-IV (hydroxy derivatives of pioglitazone) and M-III (keto derivative of pioglitazone) are pharmacologically active in animal models of type 2 diabetes. In addition to pioglitazone, M-III and M-IV are the principal drug-related species found in human serum following multiple dosing. At steady-state, in both healthy volunteers and in patients with type 2 diabetes, pioglitazone comprises approximately 30% to 50% of the total peak serum concentrations and 20% to 25% of the total AUC.

In vitro data demonstrate that multiple CYP isoforms are involved in the metabolism of pioglitazone. The cytochrome P450 isoforms involved are CYP2C8 and, to a lesser degree, CYP3A4 with additional contributions from a variety of other isoforms including the mainly extrahepatic CYP1A1. In vivo studies of pioglitazone in combination with P450 inhibitors and substrates have been performed (see PRECAUTIONS, Drug Interactions, Pioglitazone hydrochloride). Urinary 6β-hydroxycortisol/cortisol ratios measured in patients treated with pioglitazone showed that pioglitazone is not a strong CYP3A4 enzyme inducer.

Following oral administration, approximately 15% to 30% of the pioglitazone dose is recovered in the urine. Renal elimination of pioglitazone is negligible and the drug is excreted primarily as metabolites and their conjugates. It is presumed that most of the oral dose is excreted into the bile either unchanged or as metabolites and eliminated in the feces.

The mean serum half-life of pioglitazone and total pioglitazone ranges from 3 to 7 hours and 16 to 24 hours, respectively. Pioglitazone has an apparent clearance, CL/F, calculated to be 5 to 7 L/hr.

Metformin hydrochloride

Intravenous single-dose studies in normal subjects demonstrate that metformin is excreted unchanged in the urine and does not undergo hepatic metabolism (no metabolites have been identified in humans) nor biliary excretion. Renal clearance is approximately 3.5 times greater than creatinine clearance which indicates that tubular secretion is the major route of metformin elimination. Following oral administration, approximately 90% of the absorbed drug is eliminated via the renal route within the first 24 hours, with a plasma elimination half-life of approximately 6.2 hours. In blood, the elimination half-life is approximately 17.6 hours, suggesting that the erythrocyte mass may be a compartment of distribution.

Special Populations

Renal Insufficiency:

Pioglitazone hydrochloride

The serum elimination half-life of pioglitazone, M-III and M-IV remains unchanged in patients with moderate (creatinine clearance 30 to 60 mL/min) to severe (creatinine clearance < 30 mL/min) renal impairment when compared to normal subjects.

Metformin hydrochloride

In patients with decreased renal function (based on creatinine clearance), the plasma and blood half-life of metformin is prolonged and the renal clearance is decreased in proportion to the decrease in creatinine clearance (see CONTRAINDICATIONS and WARNINGS, Metformin hydrochloride, also see GLUCOPHAGE® prescribing information, CLINICAL PHARMACOLOGY, Pharmacokinetics). Since metformin is contraindicated in patients with renal impairment, ACTOPLUS MET is also contraindicated in these patients.

Hepatic Insufficiency:

Pioglitazone hydrochloride

Compared with normal controls, subjects with impaired hepatic function (Child-Pugh Grade B/C) have an approximate 45% reduction in pioglitazone and total pioglitazone mean peak concentrations but no change in the mean AUC values.

Therapy with ACTOPLUS MET should not be initiated if the patient exhibits clinical evidence of active liver disease or serum transaminase levels (ALT) exceed 2.5 times the upper limit of normal (see PRECAUTIONS, General: Pioglitazone hydrochloride).

Metformin hydrochloride

No pharmacokinetic studies of metformin have been conducted in subjects with hepatic insufficiency.

Elderly:

Pioglitazone hydrochloride

In healthy elderly subjects, peak serum concentrations of pioglitazone and total pioglitazone are not significantly different, but AUC values are slightly higher and the terminal half-life values slightly longer than for younger subjects. These changes were not of a magnitude that would be considered clinically relevant.

Metformin hydrochloride

Limited data from controlled pharmacokinetic studies of metformin in healthy elderly subjects suggest that total plasma clearance is decreased, the half-life is prolonged, and Cmax is increased, compared to healthy young subjects. From these data, it appears that the change in metformin pharmacokinetics with aging is primarily accounted for by a change in renal function (see GLUCOPHAGE® prescribing information, CLINICAL PHARMACOLOGY, Special Populations, Geriatrics).

ACTOPLUS MET treatment should not be initiated in patients ≥ 80 years of age unless measurement of creatinine clearance demonstrates that renal function is not reduced (see WARNINGS, Metformin hydrochloride and DOSAGE AND ADMINISTRATION; also see GLUCOPHAGE® prescribing information).

Pediatrics:

Pioglitazone hydrochloride

Pharmacokinetic data in the pediatric population are not available.

Metformin hydrochloride

After administration of a single oral metformin 500 mg tablet with food, geometric mean metformin Cmax and AUC differed less than 5% between pediatric type 2 diabetic patients (12 to 16 years of age) and gender- and weight-matched healthy adults (20 to 45 years of age), and all with normal renal function.

Gender:

Pioglitazone hydrochloride

As monotherapy and in combination with sulfonylurea, metformin, or insulin, pioglitazone improved glycemic control in both males and females. The mean Cmax and AUC values were increased 20% to 60% in females. In controlled clinical trials, hemoglobin A1C (A1C) decreases from baseline were generally greater for females than for males (average mean difference in A1C 0.5%). Since therapy should be individualized for each patient to achieve glycemic control, no dose adjustment is recommended based on gender alone.

Metformin hydrochloride

Metformin pharmacokinetic parameters did not differ significantly between normal subjects and patients with type 2 diabetes when analyzed according to gender (males = 19, females = 16). Similarly, in controlled clinical studies in patients with type 2 diabetes, the antihyperglycemic effect of metformin was comparable in males and females.

Ethnicity:

Pioglitazone hydrochloride

Pharmacokinetic data among various ethnic groups are not available.

Metformin hydrochloride

No studies of metformin pharmacokinetic parameters according to race have been performed. In controlled clinical studies of metformin in patients with type 2 diabetes, the antihyperglycemic effect was comparable in whites (n=249), blacks (n=51), and Hispanics (n=24).

Drug-Drug Interactions

Co-administration of a single dose of metformin (1000 mg) and pioglitazone after 7 days of pioglitazone (45 mg) did not alter the pharmacokinetics of the single dose of metformin. Specific pharmacokinetic drug interaction studies with ACTOPLUS MET have not been performed, although such studies have been conducted with the individual pioglitazone and metformin components.

Pioglitazone hydrochloride

The following drugs were studied in healthy volunteers with co-administration of pioglitazone 45 mg once daily. Results are listed below:

Oral Contraceptives: Co-administration of pioglitazone (45 mg once daily) and an oral contraceptive (1 mg norethindrone plus 0.035 mg ethinyl estradiol once daily) for 21 days, resulted in 11% and 11-14% decrease in ethinyl estradiol AUC (0-24h) and Cmax respectively. There were no significant changes in norethindrone AUC (0-24h) and Cmax. In view of the high variability of ethinyl estradiol pharmacokinetics, the clinical significance of this finding is unknown.

Midazolam: Administration of pioglitazone for 15 days followed by a single 7.5 mg dose of midazolam syrup resulted in a 26% reduction in midazolam Cmax and AUC.

Nifedipine ER: Co-administration of pioglitazone for 7 days with 30 mg nifedipine ER administered orally once daily for 4 days to male and female volunteers resulted in a ratio of least square mean (90% CI) values for unchanged nifedipine of 0.83 (0.73 - 0.95) for Cmax and 0.88 (0.80 - 0.96) for AUC. In view of the high variability of nifedipine pharmacokinetics, the clinical significance of this finding is unknown.

Ketoconazole: Co-administration of pioglitazone for 7 days with ketoconazole 200 mg administered twice daily resulted in a ratio of least square mean (90% CI) values for unchanged pioglitazone of 1.14 (1.06 - 1.23) for Cmax, 1.34 (1.26 - 1.41) for AUC and 1.87 (1.71 - 2.04) for Cmin.

Atorvastatin Calcium: Co-administration of pioglitazone for 7 days with atorvastatin calcium (LIPITOR®) 80 mg once daily resulted in a ratio of least square mean (90% CI) values for unchanged pioglitazone of 0.69 (0.57 - 0.85) for Cmax, 0.76 (0.65 - 0.88) for AUC and 0.96 (0.87 - 1.05) for Cmin. For unchanged atorvastatin the ratio of least square mean (90% CI) values were 0.77 (0.66 - 0.90) for Cmax, 0.86 (0.78 - 0.94) for AUC and 0.92 (0.82 - 1.02) for Cmin.

Cytochrome P450: See PRECAUTIONS, Drug Interactions, Pioglitazone hydrochloride

Gemfibrozil: Concomitant administration of gemfibrozil (oral 600 mg twice daily), an inhibitor of CYP2C8, with pioglitazone (oral 30 mg) in 10 healthy volunteers pre-treated for 2 days prior with gemfibrozil (oral 600 mg twice daily) resulted in pioglitazone exposure (AUC0-24) being 226% of the pioglitazone exposure in the absence of gemfibrozil (see PRECAUTIONS, Drug Interactions, Pioglitazone hydrochloride).^1

Rifampin: Concomitant administration of rifampin (oral 600 mg once daily), an inducer of CYP2C8 with pioglitazone (oral 30 mg) in 10 healthy volunteers pre-treated for 5 days prior with rifampin (oral 600 mg once daily) resulted in a decrease in the AUC of pioglitazone by 54% (see PRECAUTIONS, Drug Interactions, Pioglitazone hydrochloride).^2

In other drug-drug interaction studies, pioglitazone had no significant effect on the pharmacokinetics of fexofenadine, glipizide, digoxin, warfarin, ranitidine HCl or theophylline.

Metformin hydrochloride

See PRECAUTIONS, Drug Interactions, Metformin hydrochloride

Pharmacodynamics and Clinical Effects

Pioglitazone hydrochloride

Clinical studies demonstrate that pioglitazone improves insulin sensitivity in insulin-resistant patients. Pioglitazone enhances cellular responsiveness to insulin, increases insulin-dependent glucose disposal, improves hepatic sensitivity to insulin, and improves dysfunctional glucose homeostasis. In patients with type 2 diabetes, the decreased insulin resistance produced by pioglitazone results in lower plasma glucose concentrations, lower plasma insulin levels, and lower A1C values. Based on results from an open-label extension study, the glucose-lowering effects of pioglitazone appear to persist for at least one year. In controlled clinical studies, pioglitazone in combination with metformin had an additive effect on glycemic control.

Patients with lipid abnormalities were included in placebo-controlled monotherapy clinical studies with pioglitazone. Overall, patients treated with pioglitazone had mean decreases in triglycerides, mean increases in HDL cholesterol, and no consistent mean changes in LDL cholesterol and total cholesterol compared to the placebo group. A similar pattern of results was seen in 16-week and 24-week combination therapy studies of pioglitazone with metformin.

Clinical Studies

There have been no clinical efficacy studies conducted with ACTOPLUS MET. However, the efficacy and safety of the separate components have been previously established and the co-administration of the separate components has been evaluated for efficacy and safety in two clinical studies. These clinical studies established an added benefit of pioglitazone in patients with inadequately controlled type 2 diabetes while on metformin therapy. Bioequivalence of ACTOPLUS MET with co-administered pioglitazone and metformin tablets was demonstrated for both ACTOPLUS MET strengths (see CLINICAL PHARMACOLOGY, Pharmacokinetics and Drug Metabolism).

Clinical Trials of Pioglitazone Add-on Therapy in Patients Not Adequately Controlled on Metformin

Two treatment-randomized, controlled clinical studies in patients with type 2 diabetes were conducted to evaluate the safety and efficacy of pioglitazone plus metformin. Both studies included patients receiving metformin, either alone or in combination with another antihyperglycemic agent, who had inadequate glycemic control. All other antihyperglycemic agents were discontinued prior to starting study treatment. In the first study, 328 patients received either 30 mg of pioglitazone or placebo once daily for 16 weeks in addition to their established metformin regimen. In the second study, 827 patients received either 30 mg or 45 mg of pioglitazone once daily for 24 weeks in addition to their established metformin regimen.

In the first study, the addition of pioglitazone 30 mg once daily to metformin treatment significantly reduced the mean A1C by 0.83% and the mean FPG by 37.7 mg/dL at Week 16 from that observed with metformin alone. In the second study, the mean reductions from Baseline at Week 24 in A1C were 0.80% and 1.01% for the 30 mg and 45 mg doses, respectively. Mean reductions from Baseline in FPG were 38.2 mg/dL and 50.7 mg/dL, respectively. Based on these reductions in A1C and FPG (Table 2), the addition of pioglitazone to metformin resulted in significant improvements in glycemic control irrespective of the metformin dose.

Table 2. Glycemic Parameters in 16-Week and 24-Week Pioglitazone Hydrochloride + Metformin Hydrochloride Combination Studies
Parameter | Placebo +metformin | Pioglitazone 30 mg + metformin
16-Week Study
A1C (%) | N=153 | N=161
Baseline mean | 9.77 | 9.92
Mean change from Baseline at 16 Weeks | 0.19 | -0.64* , †
Difference in change from placebo + metformin |  | -0.83
Responder rate (%) (a) | 21.6 | 54.0
FPG (mg/dL) | N=157 | N=165
Baseline mean | 259.9 | 254.4
Mean change from Baseline at 16 Weeks | -5.2 | -42.8* , †
Difference in change from placebo + metformin |  | -37.7
Responder rate (%) (b) | 23.6 | 59.4
Parameter | Pioglitazone 30 mg + metformin | Pioglitazone 45 mg + metformin
24-Week Study
A1C (%) | N=400 | N=398
Baseline mean | 9.88 | 9.81
Mean Change from Baseline at 24 Weeks | -0.80* | -1.01*
Responder rate (%) (a) | 55.8 | 63.3
FPG (mg/dL) | N=398 | N=399
Baseline mean | 232.5 | 232.1
Mean Change from Baseline at 24 Weeks | -38.2* | -50.7* , ‡
Responder rate (%) (b) | 52.3 | 63.7
* significant change from Baseline p ≤ 0.050.
† significant difference from placebo plus metformin, p ≤ 0.050.
‡ significant difference from 30 mg pioglitazone, p ≤ 0.050.
(a) patients who achieved an A1C ≤ 6.1% or ≥ 0.6% decrease from Baseline.
(b) patients who achieved a decrease in FPG by ≥ 30 mg/dL.

INDICATIONS AND USAGE

ACTOPLUS MET is a thiazolidinedione and biguanide combination product indicated as an adjunct to diet and exercise to improve glycemic control in adults with type 2 diabetes mellitus who are already treated with a thiazolidinedione and metformin or who have inadequate glycemic control on a thiazolidinedione alone or metformin alone.

CONTRAINDICATIONS

Initiation of ACTOPLUS MET in patients with established New York Heart Association (NYHA) Class III or IV heart failure is contraindicated (see BOXED WARNING).

In addition, ACTOPLUS MET is contraindicated in patients with:

1. Renal disease or renal dysfunction (e.g., as suggested by serum creatinine levels ≥ 1.5 mg/dL [males], ≥ 1.4 mg/dL [females], or abnormal creatinine clearance) which may also result from conditions such as cardiovascular collapse (shock), acute myocardial infarction, and septicemia (see WARNINGS, Metformin hydrochloride and PRECAUTIONS, General: Metformin hydrochloride).
2. Known hypersensitivity to pioglitazone, metformin or any other component of ACTOPLUS MET.
3. Acute or chronic metabolic acidosis, including diabetic ketoacidosis, with or without coma. Diabetic ketoacidosis should be treated with insulin.

ACTOPLUS MET should be temporarily discontinued in patients undergoing radiologic studies involving intravascular administration of iodinated contrast materials, because use of such products may result in acute alteration of renal function (see PRECAUTIONS, General: Metformin hydrochloride).

WARNINGS

Metformin hydrochloride

Lactic Acidosis: Lactic acidosis is a rare, but serious, metabolic complication that can occur due to metformin accumulation during treatment with ACTOPLUS MET (pioglitazone hydrochloride and metformin hydrochloride) tablets; when it occurs, it is fatal in approximately 50% of cases. Lactic acidosis may also occur in association with a number of pathophysiologic conditions, including diabetes mellitus, and whenever there is significant tissue hypoperfusion and hypoxemia. Lactic acidosis is characterized by elevated blood lactate levels (> 5 mmol/L), decreased blood pH, electrolyte disturbances with an increased anion gap, and an increased lactate/pyruvate ratio. When metformin is implicated as the cause of lactic acidosis, metformin plasma levels > 5 µg/mL are generally found.

The reported incidence of lactic acidosis in patients receiving metformin hydrochloride is very low (approximately 0.03 cases/1000 patient-years, with approximately 0.015 fatal cases/1000 patient-years). In more than 20,000 patient-years exposure to metformin in clinical trials, there were no reports of lactic acidosis. Reported cases have occurred primarily in diabetic patients with significant renal insufficiency, including both intrinsic renal disease and renal hypoperfusion, often in the setting of multiple concomitant medical/surgical problems and multiple concomitant medications. Patients with congestive heart failure requiring pharmacologic management, in particular those with unstable or acute congestive heart failure who are at risk of hypoperfusion and hypoxemia, are at increased risk of lactic acidosis. The risk of lactic acidosis increases with the degree of renal dysfunction and the patient's age. The risk of lactic acidosis may, therefore, be significantly decreased by regular monitoring of renal function in patients taking metformin and by use of the minimum effective dose of metformin. In particular, treatment of the elderly should be accompanied by careful monitoring of renal function. Metformin treatment should not be initiated in patients ≥ 80 years of age unless measurement of creatinine clearance demonstrates that renal function is not reduced, as these patients are more susceptible to developing lactic acidosis. In addition, metformin should be promptly withheld in the presence of any condition associated with hypoxemia, dehydration, or sepsis. Because impaired hepatic function may significantly limit the ability to clear lactate, metformin should generally be avoided in patients with clinical or laboratory evidence of hepatic disease. Patients should be cautioned against excessive alcohol intake, either acute or chronic, when taking metformin, since alcohol potentiates the effects of metformin hydrochloride on lactate metabolism. In addition, metformin should be temporarily discontinued prior to any intravascular radiocontrast study and for any surgical procedure (see PRECAUTIONS, General: Metformin hydrochloride).

The onset of lactic acidosis often is subtle, and accompanied only by nonspecific symptoms such as malaise, myalgias, respiratory distress, increasing somnolence, and nonspecific abdominal distress. There may be associated hypothermia, hypotension, and resistant bradyarrhythmias with more marked acidosis. The patient and the patient's physician must be aware of the possible importance of such symptoms and the patient should be instructed to notify the physician immediately if they occur (see PRECAUTIONS, General: Metformin hydrochloride). Metformin should be withdrawn until the situation is clarified. Serum electrolytes, ketones, blood glucose, and, if indicated, blood pH, lactate levels, and even blood metformin levels may be useful. Once a patient is stabilized on any dose level of metformin, gastrointestinal symptoms, which are common during initiation of therapy, are unlikely to be drug related. Later occurrence of gastrointestinal symptoms could be due to lactic acidosis or other serious disease.

Levels of fasting venous plasma lactate above the upper limit of normal but less than 5 mmol/L in patients taking metformin do not necessarily indicate impending lactic acidosis and may be explainable by other mechanisms, such as poorly controlled diabetes or obesity, vigorous physical activity, or technical problems in sample handling (see PRECAUTIONS, General: Metformin hydrochloride).

Lactic acidosis should be suspected in any diabetic patient with metabolic acidosis lacking evidence of ketoacidosis (ketonuria and ketonemia).

Lactic acidosis is a medical emergency that must be treated in a hospital setting. In a patient with lactic acidosis who is taking metformin, the drug should be discontinued immediately and general supportive measures promptly instituted. Because metformin hydrochloride is dialyzable (with a clearance of up to 170 mL/min under good hemodynamic conditions), prompt hemodialysis is recommended to correct the acidosis and remove the accumulated metformin. Such management often results in prompt reversal of symptoms and recovery (see CONTRAINDICATIONS and PRECAUTIONS, General: Metformin hydrochloride).

Pioglitazone hydrochloride

Cardiac Failure and Other Cardiac Effects: Pioglitazone, like other thiazolidinediones, can cause fluid retention when used alone or in combination with other antihyperglycemic agents, including insulin. Fluid retention may lead to or exacerbate heart failure. Patients should be observed for signs and symptoms of heart failure. If these signs and symptoms develop, the heart failure should be managed according to current standards of care. Furthermore, discontinuation or dose reduction of pioglitazone must be considered. Patients with NYHA Class III and IV cardiac status were not studied during pre-approval clinical trials and pioglitazone is not recommended in these patients (see BOXED WARNING and CONTRAINDICATIONS).

In one 16-week U.S. double-blind, placebo-controlled clinical trial involving 566 patients with type 2 diabetes, pioglitazone at doses of 15 mg and 30 mg in combination with insulin was compared to insulin therapy alone. This trial included patients with long-standing diabetes and a high prevalence of pre-existing medical conditions as follows: arterial hypertension (57.2%), peripheral neuropathy (22.6%), coronary heart disease (19.6%), retinopathy (13.1%), myocardial infarction (8.8%), vascular disease (6.4%), angina pectoris (4.4%), stroke and/or transient ischemic attack (4.1%), and congestive heart failure (2.3%).

In this study two of the 191 patients receiving 15 mg pioglitazone plus insulin (1.1%) and two of the 188 patients receiving 30 mg pioglitazone plus insulin (1.1%) developed congestive heart failure compared with none of the 187 patients on insulin therapy alone. All four of these patients had previous histories of cardiovascular conditions including coronary artery disease, previous CABG procedures, and myocardial infarction. In a 24-week dose-controlled study in which pioglitazone was co-administered with insulin, 0.3% of patients (1/345) on 30 mg and 0.9% (3/345) of patients on 45 mg reported CHF as a serious adverse event.

Analysis of data from these studies did not identify specific factors that predict increased risk of congestive heart failure on combination therapy with insulin.

In type 2 diabetes and congestive heart failure (systolic dysfunction)

A 24-week post-marketing safety study was performed to compare ACTOS (n=262) to glyburide (n=256) in uncontrolled diabetic patients (mean A1C 8.8% at baseline) with NYHA Class II and III heart failure and ejection fraction less than 40% (mean EF 30% at baseline). Over the course of the study, overnight hospitalization for congestive heart failure was reported in 9.9% of patients on ACTOS compared to 4.7% of patients on glyburide with a treatment difference observed from 6 weeks. This adverse event associated with ACTOS was more marked in patients using insulin at baseline and in patients over 64 years of age. No difference in cardiovascular mortality between the treatment groups was observed.

ACTOS should be initiated at the lowest approved dose if it is prescribed for patients with type 2 diabetes and systolic heart failure (NYHA Class II). If subsequent dose escalation is necessary, the dose should be increased gradually only after several months of treatment with careful monitoring for weight gain, edema, or signs and symptoms of CHF exacerbation.

Prospective Pioglitazone Clinical Trial In Macrovascular Events (PROactive)

In PROactive, 5238 patients with type 2 diabetes and a prior history of macrovascular disease were treated with ACTOS (n=2605), force-titrated up to 45 mg once daily, or placebo (n=2633) (see ADVERSE REACTIONS). The percentage of patients who had an event of serious heart failure was higher for patients treated with ACTOS (5.7%, n=149) than for patients treated with placebo (4.1%, n=108). The incidence of death subsequent to a report of serious heart failure was 1.5% (n=40) in patients treated with ACTOS and 1.4% (n=37) in placebo-treated patients. In patients treated with an insulin-containing regimen at baseline, the incidence of serious heart failure was 6.3% (n=54/864) with ACTOS and 5.2% (n=47/896) with placebo. For those patients treated with a sulfonylurea-containing regimen at baseline, the incidence of serious heart failure was 5.8% (n=94/1624) with ACTOS and 4.4% (n=71/1626) with placebo.

PRECAUTIONS

General: Pioglitazone hydrochloride

Pioglitazone exerts its antihyperglycemic effect only in the presence of insulin. Therefore, ACTOPLUS MET should not be used in patients with type 1 diabetes or for the treatment of diabetic ketoacidosis.

Hypoglycemia: Patients receiving pioglitazone in combination with insulin or oral hypoglycemic agents may be at risk for hypoglycemia, and a reduction in the dose of the concomitant agent may be necessary.

Cardiovascular: In U.S. placebo-controlled clinical trials that excluded patients with New York Heart Association (NYHA) Class III and IV cardiac status, the incidence of serious cardiac adverse events related to volume expansion was not increased in patients treated with pioglitazone as monotherapy or in combination with sulfonylureas or metformin vs. placebo-treated patients. In insulin combination studies, a small number of patients with a history of previously existing cardiac disease developed congestive heart failure when treated with pioglitazone in combination with insulin (see WARNINGS, Pioglitazone hydrochloride). Patients with NYHA Class III and IV cardiac status were not studied in pre-approval pioglitazone clinical trials. Pioglitazone is not indicated in patients with NYHA Class III or IV cardiac status.

In postmarketing experience with pioglitazone, cases of congestive heart failure have been reported in patients both with and without previously known heart disease.

Edema: In all U.S. clinical trials with pioglitazone, edema was reported more frequently in patients treated with pioglitazone than in placebo-treated patients and appears to be dose related (see ADVERSE REACTIONS). In postmarketing experience, reports of initiation or worsening of edema have been received. Since thiazolidinediones, including pioglitazone, can cause fluid retention, which can exacerbate or lead to congestive heart failure, ACTOPLUS MET should be used with caution in patients at risk for heart failure. Patients should be monitored for signs and symptoms of heart failure (see BOXED WARNING, WARNINGS, Pioglitazone hydrochloride, and PRECAUTIONS, Information for Patients).

Weight Gain: Dose related weight gain was observed with pioglitazone alone and in combination with other hypoglycemic agents (Table 3). The mechanism of weight gain is unclear but probably involves a combination of fluid retention and fat accumulation.

Table 3. Weight Changes (kg) from Baseline during Double-Blind Clinical Trials with Pioglitazone
 |  |  | Control Group | pioglitazone 15 mg | pioglitazone 30 mg | pioglitazone 45 mg
 |  |  | Median (25th/75th percentile) | Median (25th/75th percentile) | Median (25th/75th percentile) | Median (25th/75th percentile)
Monotherapy |  |  | -1.4 (-2.7/0.0) n=256 | 0.9 (-0.5/3.4) n = 79 | 1.0 (-0.9/3.4) n=188 | 2.6 (0.2/5.4) n = 79
Combination Therapy |  | Sulfonylurea | -0.5 (-1.8/0.7) n=187 | 2.0 (0.2/3.2) n=183 | 3.1 (1.1/5.4) n=528 | 4.1 (1.8/7.3) n=333
 |  | Metformin | -1.4 (-3.2/0.3) n=160 | N/A | 0.9 (-0.3/3.2) n=567 | 1.8 (-0.9/5.0) n=407
 |  | Insulin | 0.2 (-1.4/1.4) n=182 | 2.3 (0.5/4.3) n=190 | 3.3 (0.9/6.3) n=522 | 4.1 (1.4/6.8) n=338
Note: Trial durations of 16 to 26 weeks

Ovulation: Therapy with pioglitazone, like other thiazolidinediones, may result in ovulation in some premenopausal anovulatory women. Thus, adequate contraception in premenopausal women should be recommended while taking ACTOPLUS MET. This possible effect has not been investigated in clinical studies so the frequency of this occurrence is not known.

Hematologic: Across all clinical studies with pioglitazone, mean hemoglobin values declined by 2% to 4% in patients treated with pioglitazone. These changes primarily occurred within the first 4 to 12 weeks of therapy and remained relatively constant thereafter. These changes may be related to increased plasma volume and have rarely been associated with any significant hematologic clinical effects (see ADVERSE REACTIONS, Laboratory Abnormalities). ACTOPLUS MET may cause decreases in hemoglobin and hematocrit.

Hepatic Effects: In pre-approval clinical studies worldwide, over 4500 subjects were treated with pioglitazone. In U.S. clinical studies, over 4700 patients with type 2 diabetes received pioglitazone. There was no evidence of drug-induced hepatotoxicity or elevation of ALT levels in the clinical studies.

During pre-approval placebo-controlled clinical trials in the U.S., a total of 4 of 1526 (0.26%) patients treated with pioglitazone and 2 of 793 (0.25%) placebo-treated patients had ALT values ≥ 3 times the upper limit of normal. The ALT elevations in patients treated with pioglitazone were reversible and were not clearly related to therapy with pioglitazone.

In postmarketing experience with pioglitazone, reports of hepatitis and of hepatic enzyme elevations to 3 or more times the upper limit of normal have been received. Very rarely, these reports have involved hepatic failure with and without fatal outcome, although causality has not been established.

Pending the availability of the results of additional large, long-term controlled clinical trials and additional postmarketing safety data on pioglitazone, it is recommended that patients treated with ACTOPLUS MET undergo periodic monitoring of liver enzymes.

Serum ALT (alanine aminotransferase) levels should be evaluated prior to the initiation of therapy with ACTOPLUS MET in all patients and periodically thereafter per the clinical judgment of the health care professional. Liver function tests should also be obtained for patients if symptoms suggestive of hepatic dysfunction occur, e.g., nausea, vomiting, abdominal pain, fatigue, anorexia, or dark urine. The decision whether to continue the patient on therapy with ACTOPLUS MET should be guided by clinical judgment pending laboratory evaluations. If jaundice is observed, drug therapy should be discontinued.

Therapy with ACTOPLUS MET should not be initiated if the patient exhibits clinical evidence of active liver disease or the ALT levels exceed 2.5 times the upper limit of normal. Patients with mildly elevated liver enzymes (ALT levels at 1 to 2.5 times the upper limit of normal) at baseline or any time during therapy with ACTOPLUS MET should be evaluated to determine the cause of the liver enzyme elevation. Initiation or continuation of therapy with ACTOPLUS MET in patients with mildly elevated liver enzymes should proceed with caution and include appropriate clinical follow-up which may include more frequent liver enzyme monitoring. If serum transaminase levels are increased (ALT > 2.5 times the upper limit of normal), liver function tests should be evaluated more frequently until the levels return to normal or pretreatment values. If ALT levels exceed 3 times the upper limit of normal, the test should be repeated as soon as possible. If ALT levels remain > 3 times the upper limit of normal or if the patient is jaundiced, ACTOPLUS MET therapy should be discontinued.

Macular Edema: Macular edema has been reported in post-marketing experience in diabetic patients who were taking pioglitazone or another thiazolidinedione. Some patients presented with blurred vision or decreased visual acuity, but some patients appear to have been diagnosed on routine ophthalmologic examination. Some patients had peripheral edema at the time macular edema was diagnosed. Some patients had improvement in their macular edema after discontinuation of their thiazolidinedione. It is unknown whether or not there is a causal relationship between pioglitazone and macular edema. Patients with diabetes should have regular eye exams by an ophthalmologist, per the Standards of Care of the American Diabetes Association. Additionally, any diabetic who reports any kind of visual symptom should be promptly referred to an ophthalmologist, regardless of the patient's underlying medications or other physical findings (see ADVERSE REACTIONS).

Fractures: In a randomized trial (PROactive) in patients with type 2 diabetes (mean duration of diabetes 9.5 years), an increased incidence of bone fracture was noted in female patients taking pioglitazone. During a mean follow-up of 34.5 months, the incidence of bone fracture in females was 5.1% (44/870) for pioglitazone versus 2.5% (23/905) for placebo. This difference was noted after the first year of treatment and remained during the course of the study. The majority of fractures observed in female patients were nonvertebral fractures including lower limb and distal upper limb. No increase in fracture rates was observed in men treated with pioglitazone 1.7% (30/1735) versus placebo 2.1% (37/1728). The risk of fracture should be considered in the care of patients, especially female patients, treated with pioglitazone and attention should be given to assessing and maintaining bone health according to current standards of care.

Macrovascular Outcomes: There have been no clinical studies establishing conclusive evidence of macrovascular risk reduction with ACTOPLUS MET or any other anti-diabetic drug.

General: Metformin hydrochloride

Monitoring of renal function: Metformin is known to be substantially excreted by the kidney, and the risk of metformin accumulation and lactic acidosis increases with the degree of impairment of renal function. Thus, patients with serum creatinine levels above the upper limit of normal for their age should not receive ACTOPLUS MET. In patients with advanced age, ACTOPLUS MET should be carefully titrated to establish the minimum dose for adequate glycemic effect, because aging is associated with reduced renal function. In elderly patients, particularly those ≥ 80 years of age, renal function should be monitored regularly and, generally, ACTOPLUS MET should not be titrated to the maximum dose of the metformin component (see WARNINGS, Metformin hydrochloride and DOSAGE AND ADMINISTRATION).

Before initiation of therapy with ACTOPLUS MET and at least annually thereafter, renal function should be assessed and verified as normal. In patients in whom development of renal dysfunction is anticipated, renal function should be assessed more frequently and ACTOPLUS MET discontinued if evidence of renal impairment is present.

Use of concomitant medications that may affect renal function or metformin disposition: Concomitant medication(s) that may affect renal function or result in significant hemodynamic change or may interfere with the disposition of metformin, such as cationic drugs that are eliminated by renal tubular secretion (see PRECAUTIONS, Drug Interactions, Metformin hydrochloride), should be used with caution.

Radiologic studies involving the use of intravascular iodinated contrast materials (for example, intravenous urogram, intravenous cholangiography, angiography, and computed tomography (CT) scans with intravascular contrast materials): Intravascular contrast studies with iodinated materials can lead to acute alteration of renal function and have been associated with lactic acidosis in patients receiving metformin (see CONTRAINDICATIONS). Therefore, in patients in whom any such study is planned, ACTOPLUS MET should be temporarily discontinued at the time of or prior to the procedure, and withheld for 48 hours subsequent to the procedure and reinstituted only after renal function has been re-evaluated and found to be normal.

Hypoxic states: Cardiovascular collapse (shock) from whatever cause, acute congestive heart failure, acute myocardial infarction and other conditions characterized by hypoxemia have been associated with lactic acidosis and may also cause prerenal azotemia. When such events occur in patients receiving ACTOPLUS MET therapy, the drug should be promptly discontinued.

Surgical procedures: Use of ACTOPLUS MET should be temporarily suspended for any surgical procedure (except minor procedures not associated with restricted intake of food and fluids) and should not be restarted until the patient's oral intake has resumed and renal function has been evaluated as normal.

Alcohol intake: Alcohol is known to potentiate the effect of metformin on lactate metabolism. Patients, therefore, should be warned against excessive alcohol intake, acute or chronic, while receiving ACTOPLUS MET.

Impaired hepatic function: Since impaired hepatic function has been associated with some cases of lactic acidosis, ACTOPLUS MET should generally be avoided in patients with clinical or laboratory evidence of hepatic disease.

Vitamin B12 levels: In controlled clinical trials of metformin at 29 weeks' duration, a decrease to subnormal levels of previously normal serum vitamin B12 levels, without clinical manifestations, was observed in approximately 7% of patients. Such decrease, possibly due to interference with B12 absorption from the B12 -intrinsic factor complex, is, however, very rarely associated with anemia and appears to be rapidly reversible with discontinuation of metformin or vitamin B12 supplementation. Measurement of hematologic parameters on an annual basis is advised in patients on ACTOPLUS MET and any apparent abnormalities should be appropriately investigated and managed (see PRECAUTIONS, General: Metformin hydrochloride and Laboratory Tests). Certain individuals (those with inadequate vitamin B12 or calcium intake or absorption) appear to be predisposed to developing subnormal vitamin B12 levels. In these patients, routine serum vitamin B12 measurements at two- to three-year intervals may be useful.

Change in clinical status of patients with previously controlled type 2 diabetes: A patient with type 2 diabetes previously well-controlled on ACTOPLUS MET who develops laboratory abnormalities or clinical illness (especially vague and poorly defined illness) should be evaluated promptly for evidence of ketoacidosis or lactic acidosis. Evaluation should include serum electrolytes and ketones, blood glucose and, if indicated, blood pH, lactate, pyruvate and metformin levels. If acidosis of either form occurs, ACTOPLUS MET must be stopped immediately and other appropriate corrective measures initiated (see WARNINGS, Metformin hydrochloride).

Hypoglycemia: Hypoglycemia does not occur in patients receiving metformin alone under usual circumstances of use, but could occur when caloric intake is deficient, when strenuous exercise is not compensated by caloric supplementation, or during concomitant use with hypoglycemic agents (such as sulfonylureas or insulin) or ethanol. Elderly, debilitated or malnourished patients and those with adrenal or pituitary insufficiency or alcohol intoxication are particularly susceptible to hypoglycemic effects. Hypoglycemia may be difficult to recognize in the elderly and in people who are taking beta-adrenergic blocking drugs.

Loss of control of blood glucose: When a patient stabilized on any diabetic regimen is exposed to stress such as fever, trauma, infection, or surgery, a temporary loss of glycemic control may occur. At such times, it may be necessary to withhold ACTOPLUS MET and temporarily administer insulin. ACTOPLUS MET may be reinstituted after the acute episode is resolved.

Laboratory Tests

FPG and A1C measurements should be performed periodically to monitor glycemic control and therapeutic response to ACTOPLUS MET.

Liver enzyme monitoring is recommended prior to initiation of therapy with ACTOPLUS MET in all patients and periodically thereafter per the clinical judgment of the health care professional (see PRECAUTIONS, General: Pioglitazone hydrochloride and ADVERSE REACTIONS, Serum Transaminase Levels).

Initial and periodic monitoring of hematologic parameters (e.g., hemoglobin/hematocrit and red blood cell indices) and renal function (serum creatinine) should be performed, at least on an annual basis. While megaloblastic anemia has rarely been seen with metformin therapy, if this is suspected, Vitamin B12 deficiency should be excluded.

Information for Patients

Patients should be instructed regarding the importance of adhering to dietary instructions, a regular exercise program, and regular testing of blood glucose and A1C. During periods of stress such as fever, trauma, infection, or surgery, medication requirements may change and patients should be reminded to seek medical advice promptly.

The risks of lactic acidosis, its symptoms and conditions that predispose to its development, as noted in the WARNINGS, Metformin hydrochloride and PRECAUTIONS, General: Metformin hydrochloride sections, should be explained to patients. Patients should be advised to discontinue ACTOPLUS MET immediately and to promptly notify their health care professional if unexplained hyperventilation, myalgia, malaise, unusual somnolence or other nonspecific symptoms occur. Gastrointestinal symptoms are common during initiation of metformin treatment and may occur during initiation of ACTOPLUS MET therapy; however, patients should consult with their physician if they develop unexplained symptoms. Although gastrointestinal symptoms that occur after stabilization are unlikely to be drug related, such an occurrence of symptoms should be evaluated to determine if it may be due to lactic acidosis or other serious disease.

Patients should be counseled against excessive alcohol intake, either acute or chronic, while receiving ACTOPLUS MET.

Patients who experience an unusually rapid increase in weight or edema or who develop shortness of breath or other symptoms of heart failure while on ACTOPLUS MET should immediately report these symptoms to their physician.

Patients should be told that blood tests for liver function will be performed prior to the start of therapy and periodically thereafter per the clinical judgment of the health care professional. Patients should be told to seek immediate medical advice for unexplained nausea, vomiting, abdominal pain, fatigue, anorexia, or dark urine.

Patients should be informed about the importance of regular testing of renal function and hematologic parameters when receiving treatment with ACTOPLUS MET.

Therapy with a thiazolidinedione, which is the active pioglitazone component of the ACTOPLUS MET tablet, may result in ovulation in some premenopausal anovulatory women. As a result, these patients may be at an increased risk for pregnancy while taking ACTOPLUS MET. Thus, adequate contraception in premenopausal women should be recommended. This possible effect has not been investigated in clinical studies so the frequency of this occurrence is not known.

Combination antihyperglycemic therapy may cause hypoglycemia. When initiating ACTOPLUS MET, the risks of hypoglycemia, its symptoms and treatment, and conditions that predispose to its development should be explained to patients.

Patients should be told to take ACTOPLUS MET as prescribed and instructed that any change in dosing should only be done if directed by their physician.

Drug Interactions

Pioglitazone hydrochloride

In vivo drug-drug interaction studies have suggested that pioglitazone may be a weak inducer of CYP450 isoform 3A4 substrate.

An enzyme inhibitor of CYP2C8 (such as gemfibrozil) may significantly increase the AUC of pioglitazone and an enzyme inducer of CYP2C8 (such as rifampin) may significantly decrease the AUC of pioglitazone. Therefore, if an inhibitor or inducer of CYP2C8 is started or stopped during treatment with pioglitazone, changes in diabetes treatment may be needed based on clinical response (see CLINICAL PHARMACOLOGY, Drug-Drug Interactions, Pioglitazone hydrochloride).

Metformin hydrochloride

Furosemide: A single-dose, metformin-furosemide drug interaction study in healthy subjects demonstrated that pharmacokinetic parameters of both compounds were affected by co-administration. Furosemide increased the metformin plasma and blood Cmax by 22% and blood AUC by 15%, without any significant change in metformin renal clearance. When administered with metformin, the Cmax and AUC of furosemide were 31% and 12% smaller, respectively, than when administered alone and the terminal half-life was decreased by 32%, without any significant change in furosemide renal clearance. No information is available about the interaction of metformin and furosemide when co-administered chronically.

Nifedipine: A single-dose, metformin-nifedipine drug interaction study in normal healthy volunteers demonstrated that co-administration of nifedipine increased plasma metformin Cmax and AUC by 20% and 9%, respectively and increased the amount excreted in the urine. Tmax and half-life were unaffected. Nifedipine appears to enhance the absorption of metformin. Metformin had minimal effects on nifedipine.

Cationic Drugs: Cationic drugs (e.g., amiloride, digoxin, morphine, procainamide, quinidine, quinine, ranitidine, triamterene, trimethoprim, and vancomycin) that are eliminated by renal tubular secretion theoretically have the potential for interaction with metformin by competing for common renal tubular transport systems. Such interaction between metformin and oral cimetidine has been observed in normal healthy volunteers in both single- and multiple-dose, metformin-cimetidine drug interaction studies with a 60% increase in peak metformin plasma and whole blood concentrations and a 40% increase in plasma and whole blood metformin AUC. There was no change in elimination half-life in the single-dose study. Metformin had no effect on cimetidine pharmacokinetics. Although such interactions remain theoretical (except for cimetidine), careful patient monitoring and dose adjustment of ACTOPLUS MET and/or the interfering drug is recommended in patients who are taking cationic medications that are excreted via the proximal renal tubular secretory system.

Other: Certain drugs tend to produce hyperglycemia and may lead to loss of glycemic control. These drugs include thiazides and other diuretics, corticosteroids, phenothiazines, thyroid products, estrogens, oral contraceptives, phenytoin, nicotinic acid, sympathomimetics, calcium channel blocking drugs, and isoniazid. When such drugs are administered to a patient receiving ACTOPLUS MET, the patient should be closely observed to maintain adequate glycemic control.

In healthy volunteers, the pharmacokinetics of metformin and propranolol and metformin and ibuprofen were not affected when co-administered in single-dose interaction studies.

Metformin is negligibly bound to plasma proteins and is therefore, less likely to interact with highly protein-bound drugs such as salicylates, sulfonamides, chloramphenicol and probenecid.

Carcinogenesis, Mutagenesis, Impairment of Fertility

ACTOPLUS MET

No animal studies have been conducted with ACTOPLUS MET. The following data are based on findings in studies performed with pioglitazone or metformin individually.

Pioglitazone hydrochloride

A two-year carcinogenicity study was conducted in male and female rats at oral doses up to 63 mg/kg (approximately 14 times the maximum recommended human oral dose of 45 mg based on mg/m^2). Drug-induced tumors were not observed in any organ except for the urinary bladder. Benign and/or malignant transitional cell neoplasms were observed in male rats at 4 mg/kg/day and above (approximately equal to the maximum recommended human oral dose based on mg/m^2). A two-year carcinogenicity study was conducted in male and female mice at oral doses up to 100 mg/kg/day (approximately 11 times the maximum recommended human oral dose based on mg/m^2). No drug-induced tumors were observed in any organ.

During prospective evaluation of urinary cytology involving more than 1800 patients receiving pioglitazone in clinical trials up to one year in duration, no new cases of bladder tumors were identified. In two 3-year studies in which pioglitazone was compared to placebo or glyburide, there were 16/3656 (0.44%) reports of bladder cancer in patients taking pioglitazone compared to 5/3679 (0.14%) in patients not taking pioglitazone. After excluding patients in whom exposure to study drug was less than one year at the time of diagnosis of bladder cancer, there were six (0.16%) cases on pioglitazone and two (0.05%) on placebo.

Pioglitazone HCl was not mutagenic in a battery of genetic toxicology studies, including the Ames bacterial assay, a mammalian cell forward gene mutation assay (CHO/HPRT and AS52/XPRT), an in vitro cytogenetics assay using CHL cells, an unscheduled DNA synthesis assay, and an in vivo micronucleus assay.

No adverse effects upon fertility were observed in male and female rats at oral doses up to 40 mg/kg pioglitazone HCl daily prior to and throughout mating and gestation (approximately 9 times the maximum recommended human oral dose based on mg/m^2).

Metformin hydrochloride

Long-term carcinogenicity studies have been performed in rats (dosing duration of 104 weeks) and mice (dosing duration of 91 weeks) at doses up to and including 900 mg/kg/day and 1500 mg/kg/day, respectively. These doses are both approximately four times a human daily dose of 2000 mg of the metformin component of ACTOPLUS MET based on body surface area comparisons. No evidence of carcinogenicity with metformin was found in either male or female mice. Similarly, there was no tumorigenic potential observed with metformin in male rats. There was, however, an increased incidence of benign stromal uterine polyps in female rats treated with 900 mg/kg/day.

There was no evidence of mutagenic potential of metformin in the following in vitro tests: Ames test (S. typhimurium), gene mutation test (mouse lymphoma cells), or chromosomal aberrations test (human lymphocytes). Results in the in vivo mouse micronucleus test were also negative.

Fertility of male or female rats was unaffected by metformin when administered at doses as high as 600 mg/kg/day, which is approximately three times the maximum recommended human daily dose of the metformin component of ACTOPLUS MET based on body surface area comparisons.

Animal Toxicology

Pioglitazone hydrochloride

Heart enlargement has been observed in mice (100 mg/kg), rats (4 mg/kg and above) and dogs (3 mg/kg) treated orally with the pioglitazone HCl component of ACTOPLUS MET (approximately 11, 1, and 2 times the maximum recommended human oral dose for mice, rats, and dogs, respectively, based on mg/m^2). In a one-year rat study, drug-related early death due to apparent heart dysfunction occurred at an oral dose of 160 mg/kg/day (approximately 35 times the maximum recommended human oral dose based on mg/m^2). Heart enlargement was seen in a 13-week study in monkeys at oral doses of 8.9 mg/kg and above (approximately 4 times the maximum recommended human oral dose based on mg/m^2), but not in a 52-week study at oral doses up to 32 mg/kg (approximately 13 times the maximum recommended human oral dose based on mg/m^2).

Pregnancy: Pregnancy Category C

ACTOPLUS MET

Because current information strongly suggests that abnormal blood glucose levels during pregnancy are associated with a higher incidence of congenital anomalies, as well as increased neonatal morbidity and mortality, most experts recommend that insulin be used during pregnancy to maintain blood glucose levels as close to normal as possible. ACTOPLUS MET should not be used during pregnancy unless the potential benefit justifies the potential risk to the fetus.

There are no adequate and well-controlled studies in pregnant women with ACTOPLUS MET or its individual components. No animal studies have been conducted with the combined products in ACTOPLUS MET. The following data are based on findings in studies performed with pioglitazone or metformin individually.

Pioglitazone hydrochloride

Pioglitazone was not teratogenic in rats at oral doses up to 80 mg/kg or in rabbits given up to 160 mg/kg during organogenesis (approximately 17 and 40 times the maximum recommended human oral dose based on mg/m^2, respectively). Delayed parturition and embryotoxicity (as evidenced by increased postimplantation losses, delayed development and reduced fetal weights) were observed in rats at oral doses of 40 mg/kg/day and above (approximately 10 times the maximum recommended human oral dose based on mg/m^2). No functional or behavioral toxicity was observed in offspring of rats. In rabbits, embryotoxicity was observed at an oral dose of 160 mg/kg (approximately 40 times the maximum recommended human oral dose based on mg/m^2). Delayed postnatal development, attributed to decreased body weight, was observed in offspring of rats at oral doses of 10 mg/kg and above during late gestation and lactation periods (approximately 2 times the maximum recommended human oral dose based on mg/m^2).

Metformin hydrochloride

Metformin was not teratogenic in rats and rabbits at doses up to 600 mg/kg/day. This represents an exposure of about two and six times a human daily dose of 2000 mg based on body surface area comparisons for rats and rabbits, respectively. Determination of fetal concentrations demonstrated a partial placental barrier to metformin.

Nursing Mothers

No studies have been conducted with the combined components of ACTOPLUS MET. In studies performed with the individual components, both pioglitazone and metformin are secreted in the milk of lactating rats. It is not known whether pioglitazone and/or metformin is secreted in human milk. Because many drugs are excreted in human milk, ACTOPLUS MET should not be administered to a breastfeeding woman. If ACTOPLUS MET is discontinued, and if diet alone is inadequate for controlling blood glucose, insulin therapy should be considered.

Pediatric Use

Safety and effectiveness of ACTOPLUS MET in pediatric patients have not been established.

Elderly Use

Pioglitazone hydrochloride

Approximately 500 patients in placebo-controlled clinical trials of pioglitazone were 65 and over. No significant differences in effectiveness and safety were observed between these patients and younger patients.

Metformin hydrochloride

Controlled clinical studies of metformin did not include sufficient numbers of elderly patients to determine whether they respond differently from younger patients, although other reported clinical experience has not identified differences in responses between the elderly and young patients. Metformin is known to be substantially excreted by the kidney and because the risk of serious adverse reactions to the drug is greater in patients with impaired renal function, ACTOPLUS MET should only be used in patients with normal renal function (see CONTRAINDICATIONS, WARNINGS, Metformin hydrochloride and CLINICAL PHARMACOLOGY, Special Populations). Because aging is associated with reduced renal function, ACTOPLUS MET should be used with caution as age increases. Care should be taken in dose selection and should be based on careful and regular monitoring of renal function. Generally, elderly patients should not be titrated to the maximum dose of ACTOPLUS MET (see WARNINGS, Metformin hydrochloride and DOSAGE AND ADMINISTRATION).

ADVERSE REACTIONS

Over 8500 patients with type 2 diabetes have been treated with pioglitazone in randomized, double-blind, controlled clinical trials. This includes 2605 high-risk patients with type 2 diabetes treated with pioglitazone from the PROactive clinical trial. Over 6000 patients have been treated for 6 months or longer, and over 4500 patients for one year or longer. Over 3000 patients have received pioglitazone for at least 2 years.

The most common adverse events reported in at least 5% of patients in the controlled 16-week clinical trial between placebo plus metformin and pioglitazone 30 mg plus metformin were upper respiratory tract infection (15.6% and 15.5%), diarrhea (6.3% and 4.8%), combined edema/peripheral edema (2.5% and 6.0%) and headache (1.9% and 6.0%), respectively.

The incidence and type of adverse events reported in at least 5% of patients in any combined treatment group from the 24-week study comparing pioglitazone 30 mg plus metformin and pioglitazone 45 mg plus metformin are shown in Table 4; the rate of adverse events resulting in study discontinuation between the two treatment groups was 7.8% and 7.7%, respectively.

Table 4. Adverse Events That Occurred in ≥ 5% of Patients in Any Treatment Group During the 24-Week Study
Adverse Event Preferred Term | Pioglitazone 30 mg + metformin N=411 n (%) | Pioglitazone 45 mg + metformin N=416 n (%)
Upper Respiratory Tract Infection | 51 (12.4) | 56 (13.5)
Diarrhea | 24 (5.8) | 20 (4.8)
Nausea | 24 (5.8) | 15 (3.6)
Headache | 19 (4.6) | 22 (5.3)
Urinary Tract Infection | 24 (5.8) | 22 (5.3)
Sinusitis | 18 (4.4) | 21 (5.0)
Dizziness | 22 (5.4) | 20 (4.8)
Edema Lower Limb | 12 (2.9) | 47 (11.3)
Weight Increased | 12 (2.9) | 28 (6.7)

Most clinical adverse events were similar between groups treated with pioglitazone in combination with metformin and those treated with pioglitazone monotherapy. Other adverse events reported in at least 5% of patients in controlled clinical trials between placebo and pioglitazone monotherapy included myalgia (2.7% and 5.4%), tooth disorder (2.3% and 5.3%), diabetes mellitus aggravated (8.1% and 5.1%) and pharyngitis (0.8% and 5.1%), respectively.

In U.S. double-blind studies, anemia was reported in ≤ 2% of patients treated with pioglitazone plus metformin (see PRECAUTIONS, General: Pioglitazone hydrochloride).

In monotherapy studies, edema was reported for 4.8% (with doses from 7.5 mg to 45 mg) of patients treated with pioglitazone versus 1.2% of placebo-treated patients. Most of these events were considered mild or moderate in intensity (see PRECAUTIONS, General: Pioglitazone hydrochloride).

Prospective Pioglitazone Clinical Trial In Macrovascular Events (PROactive)

In PROactive, 5238 patients with type 2 diabetes and a prior history of macrovascular disease were treated with ACTOS (n=2605), force-titrated up to 45 mg daily, or placebo (n=2633), in addition to standard of care. Almost all subjects (95%) were receiving cardiovascular medications (beta blockers, ACE inhibitors, ARBs, calcium channel blockers, nitrates, diuretics, aspirin, statins, fibrates). Patients had a mean age of 61.8 years, mean duration of diabetes 9.5 years, and mean A1C 8.1%. Average duration of follow-up was 34.5 months. The primary objective of this trial was to examine the effect of ACTOS on mortality and macrovascular morbidity in patients with type 2 diabetes mellitus who were at high risk for macrovascular events. The primary efficacy variable was the time to the first occurrence of any event in the cardiovascular composite endpoint (see table 5 below). Although there was no statistically significant difference between ACTOS and placebo for the 3-year incidence of a first event within this composite, there was no increase in mortality or in total macrovascular events with ACTOS.

Table 5 Number of First and Total Events for Each Component within the Cardiovascular Composite Endpoint
 | Placebo N=2633 |  | ACTOS N=2605
Cardiovascular Events | First Events (N) | Total events (N) | First Events (N) | Total events (N)
Any event | 572 | 900 | 514 | 803
All-cause mortality | 122 | 186 | 110 | 177
Non-fatal MI | 118 | 157 | 105 | 131
Stroke | 96 | 119 | 76 | 92
ACS | 63 | 78 | 42 | 65
Cardiac intervention | 101 | 240 | 101 | 195
Major leg amputation | 15 | 28 | 9 | 28
Leg revascularization | 57 | 92 | 71 | 115

Postmarketing reports of new onset or worsening diabetic macular edema with decreased visual acuity have also been received (see PRECAUTIONS, General: Pioglitazone hydrochloride).

Laboratory Abnormalities

Hematologic: Pioglitazone may cause decreases in hemoglobin and hematocrit. The fall in hemoglobin and hematocrit with pioglitazone appears to be dose related. Across all clinical studies, mean hemoglobin values declined by 2% to 4% in patients treated with pioglitazone. These changes generally occurred within the first 4 to 12 weeks of therapy and remained relatively stable thereafter. These changes may be related to increased plasma volume associated with pioglitazone therapy and have rarely been associated with any significant hematologic clinical effects (see PRECAUTIONS, General: Pioglitazone hydrochloride).

In controlled clinical trials of metformin at 29 weeks' duration, a decrease to subnormal levels of previously normal serum vitamin B12 levels, without clinical manifestations, was observed in approximately 7% of patients. Such decrease, possibly due to interference with B12 absorption from the B12 -intrinsic factor complex, is, however, very rarely associated with anemia and appears to be rapidly reversible with discontinuation of metformin or vitamin B12 supplementation (see PRECAUTIONS, General: Metformin hydrochloride).

Serum Transaminase Levels: During all clinical studies in the U.S., 14 of 4780 (0.30%) patients treated with pioglitazone had ALT values ≥ 3 times the upper limit of normal during treatment. All patients with follow-up values had reversible elevations in ALT. In the population of patients treated with pioglitazone, mean values for bilirubin, AST, ALT, alkaline phosphatase, and GGT were decreased at the final visit compared with baseline. Fewer than 0.9% of patients treated with pioglitazone were withdrawn from clinical trials in the U.S. due to abnormal liver function tests.

In pre-approval clinical trials, there were no cases of idiosyncratic drug reactions leading to hepatic failure (see PRECAUTIONS, General: Pioglitazone hydrochloride).

CPK Levels: During required laboratory testing in clinical trials with pioglitazone, sporadic, transient elevations in creatine phosphokinase levels (CPK) were observed. An isolated elevation to greater than 10 times the upper limit of normal was noted in 9 patients (values of 2150 to 11400 IU/L). Six of these patients continued to receive pioglitazone, two patients had completed receiving study medication at the time of the elevated value and one patient discontinued study medication due to the elevation. These elevations resolved without any apparent clinical sequelae. The relationship of these events to pioglitazone therapy is unknown.

OVERDOSAGE

Pioglitazone hydrochloride

During controlled clinical trials, one case of overdose with pioglitazone was reported. A male patient took 120 mg per day for four days, then 180 mg per day for seven days. The patient denied any clinical symptoms during this period.

In the event of overdosage, appropriate supportive treatment should be initiated according to patient's clinical signs and symptoms.

Metformin hydrochloride

Overdose of metformin hydrochloride has occurred, including ingestion of amounts greater than 50 grams. Hypoglycemia was reported in approximately 10% of cases, but no causal association with metformin hydrochloride has been established. Lactic acidosis has been reported in approximately 32% of metformin overdose cases (see WARNINGS, Metformin hydrochloride). Metformin is dialyzable with a clearance of up to 170 mL/min under good hemodynamic conditions. Therefore, hemodialysis may be useful for removal of accumulated metformin from patients in whom metformin overdosage is suspected.

DOSAGE AND ADMINISTRATION

General

The use of antihyperglycemic therapy in the management of type 2 diabetes should be individualized on the basis of effectiveness and tolerability while not exceeding the maximum recommended daily dose of pioglitazone 45 mg and metformin 2550 mg.

Dosage Recommendations

Selecting the starting dose of ACTOPLUS MET should be based on the patient's current regimen of pioglitazone and/or metformin. After initiation of ACTOPLUS MET or with dose increase, patients should be carefully monitored for adverse events related to fluid retention (see BOXED WARNING and WARNINGS, Pioglitazone hydrochloride). ACTOPLUS MET should be given in divided daily doses with meals to reduce the gastrointestinal side effects associated with metformin.

Starting dose for patients inadequately controlled on metformin monotherapy

Based on the usual starting dose of pioglitazone (15-30 mg daily), ACTOPLUS MET may be initiated at either the 15 mg/500 mg or 15 mg/850 mg tablet strength once or twice daily, and gradually titrated after assessing adequacy of therapeutic response.

Starting dose for patients who initially responded to pioglitazone monotherapy and require additional glycemic control

Based on the usual starting doses of metformin (500 mg twice daily or 850 mg daily), ACTOPLUS MET may be initiated at either the 15 mg/500 mg twice daily or 15 mg/850 mg tablet strength once daily, and gradually titrated after assessing adequacy of therapeutic response.

Starting dose for patients switching from combination therapy of pioglitazone plus metformin as separate tablets

ACTOPLUS MET may be initiated with either the 15 mg/500 mg or 15 mg/850 mg tablet strengths based on the dose of pioglitazone and metformin already being taken.

No studies have been performed specifically examining the safety and efficacy of ACTOPLUS MET in patients previously treated with other oral hypoglycemic agents and switched to ACTOPLUS MET. Any change in therapy of type 2 diabetes should be undertaken with care and appropriate monitoring as changes in glycemic control can occur.

Sufficient time should be given to assess adequacy of therapeutic response. Ideally, the response to therapy should be evaluated using A1C, which is a better indicator of long-term glycemic control than FPG alone. A1C reflects glycemia over the past two to three months. In clinical use, it is recommended that patients be treated with ACTOPLUS MET for a period of time adequate to evaluate change in A1C (8-12 weeks) unless glycemic control as measured by FPG deteriorates.

Special Patient Populations

ACTOPLUS MET is not recommended for use in pregnancy or for use in pediatric patients.

The initial and maintenance dosing of ACTOPLUS MET should be conservative in patients with advanced age, due to the potential for decreased renal function in this population. Any dosage adjustment should be based on a careful assessment of renal function. Generally, elderly, debilitated, and malnourished patients should not be titrated to the maximum dose of ACTOPLUS MET. Monitoring of renal function is necessary to aid in prevention of metformin-associated lactic acidosis, particularly in the elderly (see WARNINGS, Metformin hydrochloride and PRECAUTIONS, General: Metformin hydrochloride).

Therapy with ACTOPLUS MET should not be initiated if the patient exhibits clinical evidence of active liver disease or increased serum transaminase levels (ALT greater than 2.5 times the upper limit of normal) at start of therapy (see PRECAUTIONS, General: Pioglitazone hydrochloride and CLINICAL PHARMACOLOGY, Special Populations, Hepatic Insufficiency). Liver enzyme monitoring is recommended in all patients prior to initiation of therapy with ACTOPLUS MET and periodically thereafter (see PRECAUTIONS, General: Pioglitazone hydrochloride and PRECAUTIONS, Laboratory Tests).

Maximum Recommended Dose

ACTOPLUS MET tablets are available as a 15 mg pioglitazone plus 500 mg metformin or a 15 mg pioglitazone plus 850 mg metformin formulation for oral administration. The maximum recommended dose for pioglitazone is 45 mg daily. The maximum recommended daily dose for metformin is 2550 mg in adults.

HOW SUPPLIED

ACTOPLUS MET is available in 15 mg pioglitazone hydrochloride (as the base)/500 mg metformin hydrochloride and 15 mg pioglitazone hydrochloride (as the base)/850 mg metformin hydrochloride tablets as follows:

15 mg/500 mg tablet: white to off-white, oblong, film-coated tablet with "4833M" on one side, and "15/500" on the other, available in:

Bottles of 30 | NDC 54868-5500-2
Bottles of 60 | NDC 54868-5500-1
Bottles of 90 | NDC 54868-5500-0

15 mg/850 mg tablet: white to off-white, oblong, film-coated tablet with "4833M" on one side, and "15/850" on the other, available in:

Bottles of 30 | NDC 54868-5553-2
Bottles of 60 | NDC 54868-5553-0
Bottles of 90 | NDC 54868-5553-1

STORAGE

Store at 25°C (77°F); excursions permitted to 15-30°C (59-86°F) [see USP Controlled Room Temperature]. Keep container tightly closed, and protect from moisture and humidity.

REFERENCES

1. Deng, LJ, et al. Effect of gemfibrozil on the pharmacokinetics of pioglitazone. Eur J Clin Pharmacol 2005; 61: 831-836, Table 1.
2. Jaakkola, T, et al. Effect of rifampicin on the pharmacokinetics of pioglitazone. Brit J Clin Pharmacol 2006; 61:1 70-78.

Rx only

ACTOS® and ACTOPLUS MET® are trademarks of Takeda Pharmaceutical Company Limited and used under license by Takeda Pharmaceuticals America, Inc.

GLUCOPHAGE® is a registered trademark of Merck Sante S.A.S., an associate of Merck KGaA of Darmstadt, Germany. Licensed to Bristol-Myers Squibb Company.

Distributed by:
Takeda Pharmaceuticals America, Inc.
Deerfield, IL 60015

©2005 Takeda Pharmaceuticals America, Inc.

December 2008
APM0808-R6

Relabeling and Repackaging by:
Physicians Total Care, Inc.
Tulsa, OK 74146

MEDICATION GUIDE

ACTOPLUS MET® (ak-TŌ-plus-met)
(pioglitazone hydrochloride and metformin hydrochloride) tablets

Read this Medication Guide carefully before you start taking ACTOPLUS MET and each time you get a refill. There may be new information. This information does not take the place of talking with your doctor about your medical condition or your treatment. If you have any questions about ACTOPLUS MET, ask your doctor or pharmacist.

What is the most important information I should know about ACTOPLUS MET?

ACTOPLUS MET can cause serious side effects, including new or worse heart failure.

- Pioglitazone, one of the medicines in ACTOPLUS MET, can cause your body to keep extra fluid (fluid retention), which leads to swelling (edema) and weight gain. Extra body fluid can make some heart problems worse or lead to heart failure. Heart failure means your heart does not pump blood well enough.
- If you have severe heart failure, you cannot start ACTOPLUS MET.
- If you have heart failure with symptoms (such as shortness of breath or swelling), even if these symptoms are not severe, ACTOPLUS MET may not be right for you.

Call your doctor right away if you have any of the following:

- swelling or fluid retention, especially in the ankles or legs.
- shortness of breath or trouble breathing, especially when you lie down.
- an unusually fast increase in weight.
- unusual tiredness.

Metformin, one of the medicines in ACTOPLUS MET, can cause a rare but serious condition called lactic acidosis (a buildup of an acid in the blood) that can cause death. Lactic acidosis is a medical emergency and must be treated in the hospital.

Most people who have had lactic acidosis with metformin have other things that, combined with the metformin, led to the lactic acidosis. Tell your doctor if you have any of the following, because you have a higher chance for getting lactic acidosis with ACTOPLUS MET if you:

- have kidney problems or your kidneys are affected by certain x-ray tests that use injectable dye. People whose kidneys are not working properly should not take ACTOPLUS MET.
- have liver problems.
- drink alcohol very often, or drink a lot of alcohol in short-term "binge" drinking.
- get dehydrated (lose a large amount of body fluids). This can happen if you are sick with a fever, vomiting, or diarrhea. Dehydration can also happen when you sweat a lot with activity or exercise and do not drink enough fluids.
- have surgery.
- have a heart attack, severe infection, or stroke.
- are 80 years of age or older, and your kidneys are not working properly.

The best way to keep from having a problem with lactic acidosis from metformin is to tell your doctor if you have any of the problems in the list above. Your doctor may decide to stop your ACTOPLUS MET for a while if you have any of these things.

Lactic acidosis can be hard to diagnose early, because the early symptoms could seem like the symptoms of many other health problems besides lactic acidosis. You should call your doctor right away if you get the following symptoms, which could be signs of lactic acidosis:

- You feel very weak or tired.
- You have unusual (not normal) muscle pain.
- You have stomach pains, nausea or vomiting.
- You have trouble breathing.
- You feel dizzy or lightheaded.
- You have a slow or irregular heartbeat.

ACTOPLUS MET can have other serious side effects. See "What are the possible side effects of ACTOPLUS MET?"

What is ACTOPLUS MET?

ACTOPLUS MET is a prescription medicine used with diet and exercise to improve blood sugar (glucose) control in adults with type 2 diabetes.

ACTOPLUS MET contains 2 prescription diabetes medicines called pioglitazone hydrochloride (ACTOS) and metformin hydrochloride (GLUCOPHAGE).

Your doctor will decide if you should take ACTOPLUS MET.

ACTOPLUS MET can be used for adults with type 2 diabetes who:

- are taking pioglitazone alone and do not have good enough blood sugar control,
- are taking metformin alone and do not have good enough blood sugar control, or
- are already taking both pioglitazone and metformin.

If you are taking pioglitazone or metformin, check with your healthcare provider and make sure you understand exactly how your healthcare provider wants you to switch over to ACTOPLUS MET.

It is important to eat the right foods, lose weight if needed, and exercise regularly in order to manage your type 2 diabetes. Diet, weight loss, and exercise are the main treatments for type 2 diabetes and they also help your diabetes medicines work better for you.

ACTOPLUS MET has not been studied in children and is not recommended for children under the age of 18. The risks of giving ACTOPLUS MET to a child are not known. See "What are some other possible side effects of ACTOPLUS MET?"

Who should not take ACTOPLUS MET?

Do not take ACTOPLUS MET if you:

- are allergic to any of the ingredients in ACTOPLUS MET. See the end of this Medication Guide for a complete list of ingredients in ACTOPLUS MET.
- have kidneys which are not working properly.
- have a condition called metabolic acidosis, including diabetic ketoacidosis. Diabetic ketoacidosis should be treated with insulin.
- are going to have an x-ray procedure with an injection of dyes (contrast agents) in your vein with a needle. Talk to your doctor about when to stop ACTOPLUS MET and when to start it again.

People with severe heart failure should not start taking ACTOPLUS MET. See "What is the most important information I should know about ACTOPLUS MET?".

What should I tell my doctor before taking ACTOPLUS MET?

Before starting ACTOPLUS MET, ask your doctor about what the choices are for diabetes medicines and what the expected benefits and possible risks are for you in particular.

Tell your doctor about all of your medical conditions, especially if you:

- have heart failure.
- have kidney problems.
- are going to have dye injected into a vein for an x-ray, CAT scan, heart study, or other type of scanning.
- drink a lot of alcohol (all the time or short binge drinking).
- have type 1 ("juvenile") diabetes or had diabetic ketoacidosis. These conditions should be treated with insulin.
- are 80 years old or older. People over 80 years should not take ACTOPLUS MET unless their kidney function is checked and it is normal.
- have a type of diabetic eye disease called macular edema (swelling of the back of the eye).
- have liver problems. Your doctor should do blood tests to check your liver before you start taking ACTOPLUS MET and during treatment as needed.
- are pregnant or planning to become pregnant. ACTOPLUS MET should not be used during pregnancy. It is not known if ACTOPLUS MET can harm your unborn baby. Talk to your doctor about the best way to control your blood glucose levels while pregnant.
- are a premenopausal woman (before the "change of life"), who does not have periods regularly or at all. ACTOPLUS MET may increase your chance of becoming pregnant. Talk to your doctor about birth control choices while taking ACTOPLUS MET. Tell your doctor right away if you become pregnant while taking ACTOPLUS MET.
- are breastfeeding or plan to breastfeed. It is not known if ACTOPLUS MET passes into your milk and if it can harm your baby. You should not take ACTOPLUS MET if you breastfeed your baby. Talk to your doctor about the best way to control your blood glucose levels while breastfeeding.

Tell your doctor about all the medicines you take including prescription and non-prescription medicines, vitamins, and herbal supplements. ACTOPLUS MET and some of your other medicines can affect each other. You may need to have your dose of ACTOPLUS MET or certain other medicines adjusted. Certain other medicines can affect your blood sugar (glucose) control.

Know the medicines you take. Keep a list of your medicines and show it to your doctor and pharmacist before you start a new medicine. They will tell you if it is okay to take ACTOPLUS MET with other medicines.

How should I take ACTOPLUS MET?

- Take ACTOPLUS MET exactly as prescribed. Your doctor will tell you how many ACTOPLUS MET tablets to take and how often you should take them. Your doctor may need to change your dose of ACTOPLUS MET to control your blood glucose. Do not change your dose unless told to do so by your doctor.
- Take ACTOPLUS MET with meals to lower your chance of an upset stomach.
- If you miss a dose of ACTOPLUS MET, take your next dose as prescribed unless your doctor tells you differently. Do not take two doses at one time the next day.
- If you take too much ACTOPLUS MET, call your doctor or poison control center right away.
- If your body is under stress, for example: due to fever, infection, trauma (such as a car accident), or surgery, the dose of your diabetes medicines may need to be changed. Call your doctor right away.
- Stay on your diet and exercise programs and test your blood sugar regularly while taking ACTOPLUS MET.
- Your doctor should do blood tests before starting ACTOPLUS MET and from time to time to check your liver, kidneys, and blood cells.
- Your doctor should also do regular blood tests (for example, hemoglobin A1C) to check how well your blood sugar is controlled with ACTOPLUS MET.
- Your doctor should check your eyes regularly. Some people have had vision changes due to swelling in the back of the eye, called macular edema, while taking ACTOPLUS MET.
- It may take 2-3 months to see the full effect on your blood sugar level.

You may need to stop ACTOPLUS MET for a short time. Call your doctor for instructions if you:

- are sick with severe vomiting, diarrhea, or fever or if you drink a much lower amount of liquid than normal.
- plan to have surgery.
- are having an x-ray procedure with injection of dye.

What are other possible side effects of ACTOPLUS MET?

ACTOPLUS MET can cause other serious side effects including:

- Weight gain. Pioglitazone, one of the medicines in ACTOPLUS MET, can cause weight gain that may be due to fluid retention or extra body fat. Weight gain due to fluid retention can be a serious problem for people with certain conditions, including heart problems. See "What is the most important information I should know about ACTOPLUS MET?".
- Liver problems. It is important for your liver to be working normally when you take ACTOPLUS MET. Your doctor should do blood tests to check your liver before you start taking ACTOPLUS MET and during treatment as needed. Call your doctor right away if you have unexplained symptoms such as:
  - nausea or vomiting.
  - stomach pain.
  - unusual or unexplained tiredness.
  - loss of appetite.
  - dark urine.
  - yellowing of your skin or the whites of your eyes.
- Macular edema (diabetic eye disease with swelling in the back of the eye). Tell your doctor right away if you have any changes in your vision. Your doctor should check your eyes regularly.
- Fractures (broken bones), usually in the hand, upper arm, or foot in women. Talk to your doctor for advice on how to keep your bones healthy. It is not known if ACTOPLUS MET can affect the bones of children.
- Low red blood cell count (anemia).
- Low blood sugar (hypoglycemia). Lightheadedness, dizziness, shakiness, or hunger may indicate that your blood sugar is too low. This can happen if you skip meals, if you use another medicine that lowers blood sugar, or if you have certain medical problems. Call your doctor if low blood sugar levels are a problem for you.
- Ovulation (release of an egg from an ovary in a woman) leading to pregnancy. Ovulation may happen when premenopausal women who do not have regular monthly periods take ACTOPLUS MET. This can increase the chance of pregnancy. See "What should I tell my doctor before taking ACTOPLUS MET?".

In studies of pioglitazone (one of the medicines in ACTOPLUS MET), bladder cancer occurred in a few more people who were taking pioglitazone than in people who were taking other diabetes medicines. There were too few cases to know if the bladder cancer was related to pioglitazone.

The most common side effects of ACTOPLUS MET reported in clinical trials included diarrhea, nausea, and upset stomach. These side effects usually happen during the first few weeks of treatment. Taking ACTOPLUS MET with meals can help lessen these side effects. However, if you have unusual or unexpected stomach problems, talk with your doctor. Stomach problems that start up later during treatment may be a sign of something more serious.

Other common side effects of ACTOPLUS MET are:

- cold-like symptoms (upper respiratory infection),
- headache,
- urinary tract infection,
- dizziness,
- sinus infection,
- anemia.

Tell your doctor if you have any side effect that bothers you or that does not go away. These are not all the side effects of ACTOPLUS MET. For more information, ask your doctor or pharmacist.

Call your doctor for medical advice about side effects. You may report side effects to FDA at 1-800-FDA-1088.

How should I store ACTOPLUS MET?

- Store ACTOPLUS MET at 59° to 86°F (15° to 30°C). Keep ACTOPLUS MET in the original container to protect from light.
- Keep the ACTOPLUS MET bottle tightly closed and protect from getting wet (away from moisture and humidity).

Keep ACTOPLUS MET and all medicines out of the reach of children.

General information about ACTOPLUS MET

Medicines are sometimes prescribed for purposes other than those listed in a Medication Guide. Do not use ACTOPLUS MET for a condition for which it is not prescribed. Do not give ACTOPLUS MET to other people, even if they have the same symptoms you have. It may harm them.

This Medication Guide summarizes the most important information about ACTOPLUS MET. If you would like more information, talk with your doctor. You can ask your doctor or pharmacist for information about ACTOPLUS MET that is written for healthcare professionals. For more information, go to www.actoplusmet.com or call 1-877-825-3327.

What are the ingredients in ACTOPLUS MET?

Active Ingredients: pioglitazone hydrochloride and metformin hydrochloride

Inactive Ingredients: povidone, microcrystalline cellulose, croscarmellose sodium, magnesium stearate, hypromellose 2910, polyethylene glycol 8000, titanium dioxide, and talc.

Always check to make sure that the medicine you are taking is the correct one. ACTOPLUS MET tablets look like this:

- 15 mg/500 mg strength tablets—white to off-white, oblong tablet with "15/500" on one side and "4833M" on the other.
- 15 mg/850 mg strength tablets—white to off-white, oblong tablet with "15/850" on one side and "4833M" on the other.

ACTOS® and ACTOPLUS MET® are registered trademarks of Takeda Pharmaceutical Company Limited and used under license by Takeda Pharmaceuticals America, Inc.

All other trademarks are the property of their respective owners.

This Medication Guide has been approved by the U.S. Food and Drug Administration.

Distributed by:
Takeda Pharmaceuticals America, Inc.
Deerfield, IL 60015

© 2009 Takeda Pharmaceuticals America, Inc.

September 2009
APM0509-R1/MG

PRINCIPAL DISPLAY PANEL 15 mg / 500 mg 60 Tablet Bottle

60 Tablets

actoplus met®

pioglitazone HCl 15 mg and
metformin HCl 500 mg tablets

Each film-coated tablet contains
pioglitazone hydrochloride
equivalent to 15 mg pioglitazone
and 500 mg metformin HCl.

Dispense with Medication Guide
available in package insert or at
www.actoplusmet.com

Rx Only

PRINCIPAL DISPLAY PANEL 15 mg / 850 mg 60 Tablet Bottle

60 Tablets

actoplus met®

pioglitazone HCl 15 mg and
metformin HCl 850 mg tablets

Each film-coated tablet contains
pioglitazone hydrochloride
equivalent to 15 mg pioglitazone
and 850 mg metformin HCl.

Dispense with Medication Guide
available in package insert or at
www.actoplusmet.com

Rx Only